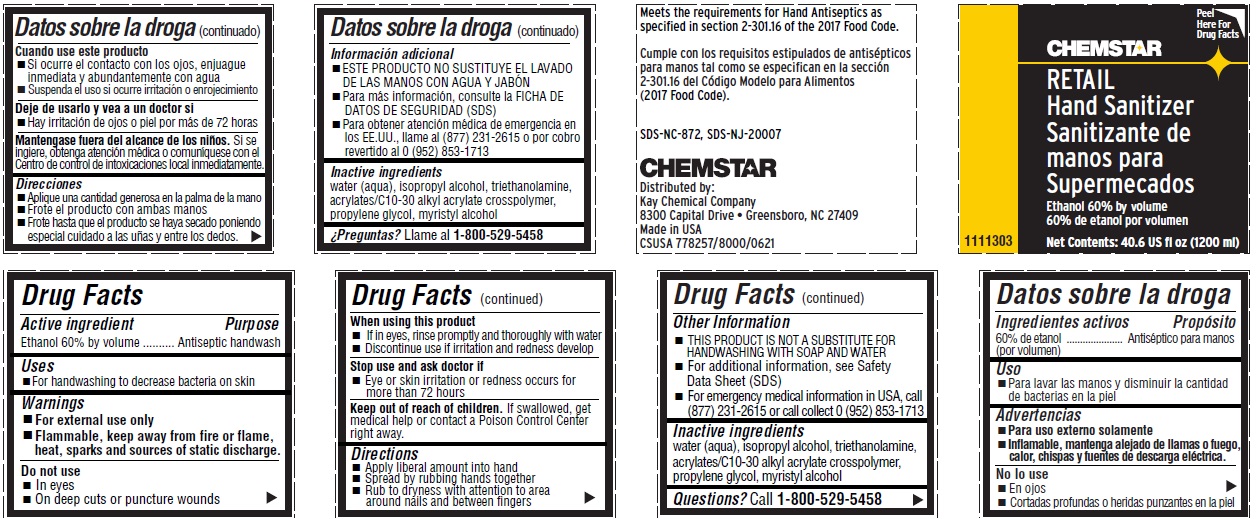 DRUG LABEL: CHEMSTAR RETAIL HAND SANITIZER
NDC: 47593-687 | Form: LIQUID
Manufacturer: Ecolab Inc.
Category: otc | Type: HUMAN OTC DRUG LABEL
Date: 20251231

ACTIVE INGREDIENTS: ALCOHOL 60 mL/100 mL
INACTIVE INGREDIENTS: ISOPROPYL ALCOHOL; TROLAMINE; CARBOMER COPOLYMER TYPE B (ALLYL PENTAERYTHRITOL CROSSLINKED); Propylene glycol; MYRISTYL ALCOHOL

Drug Facts

Active ingredient

Ethanol 60% by volume

Purpose

Antiseptic handwash

Uses

- For handwashing to decrease bacteria on the skin

Warnings

- For external use only
- FLAMMABLE, keep away from fire or flame, heat, sparks and sources of static discharge

Do not use

- In eyes
- On deep cuts or puncture wounds

When using this product

- If in eyes, rinse promptly and thoroughly with water
- Discontinue use if irritation and redness develop

Stop use and ask a doctor if

- eye or skin irritation or redness occurs for more than 72 hours

Keep out of reach of children.

- If swallowed, get medical help or contact a Poison Control Center right away.

Directions

- Apply liberal amount into hand
- Spread by rubbing hands together
- Rub to dryness with attention to area around nails and between fingers

Other information

- THIS PRODUCT IS NOT A SUBSTITUTE FOR HANDWASHINGWITH SOAP AND WATER
- For additional information, see Safety Data Sheet (SDS)
- For emergency health information in USA, call (877) 231-2615 or call collect 0 (952) 853-1713

INACTIVE INGREDIENT

Inactive ingredients water (aqua), isopropyl alcohol, triethanolamine, acrylates/C10-30 alkyl acrylate crosspolymer, propylene glycol, myristyl alcohol

Questions? call 1-800-529-5458

Principal display panel and representative label

CHEMSTAR

RETAIL

Hand Sanitizer

Sanitizante de

manos para

Supermecados

Ethanol 60% by volume

60% de etanol por volume

1111303

Net Contents: 40.6 US fl oz (1200 ml)

Meets the requirements for Hand Antiseptics as

specified in section 2-301.16 of the 2017 Food Code.

Cumple con los requisitos estipulados de antisépticos

para manos tal como se especifican en la sección

2-301.16 del Código Modelo para Alimentos

(2017 Food Code).

SDS-NC-872, SDS-NJ-20007

CHEMSTAR

Distributed by:

Kay Chemical Company

8300 Capital Drive • Greensboro, NC 27409

Made in USA

CSUSA 778257/8000/0621